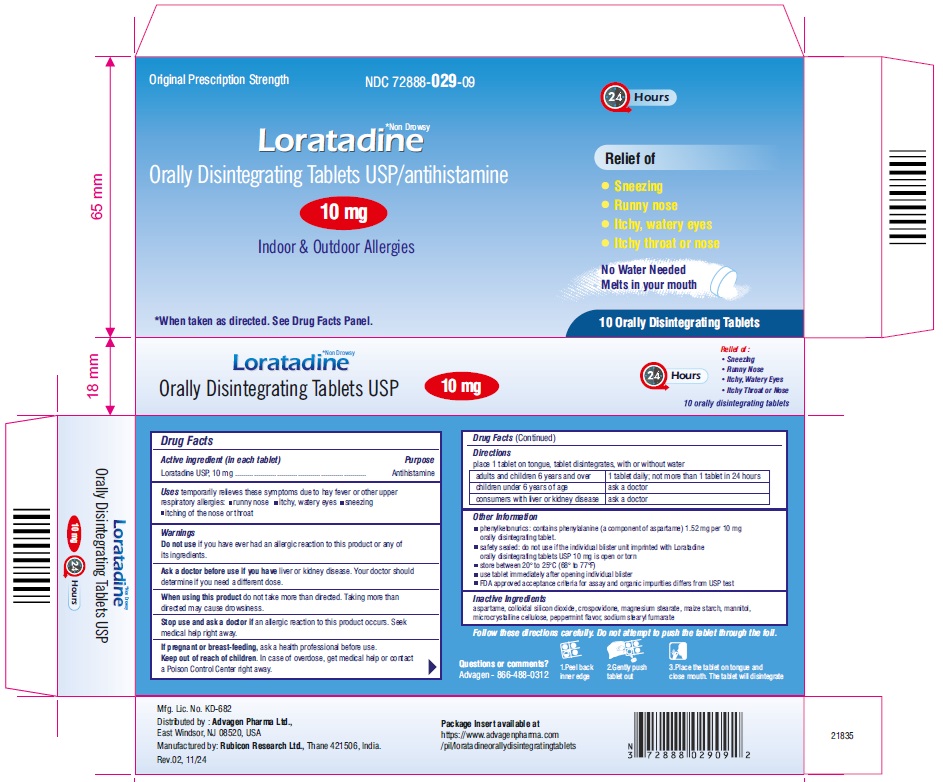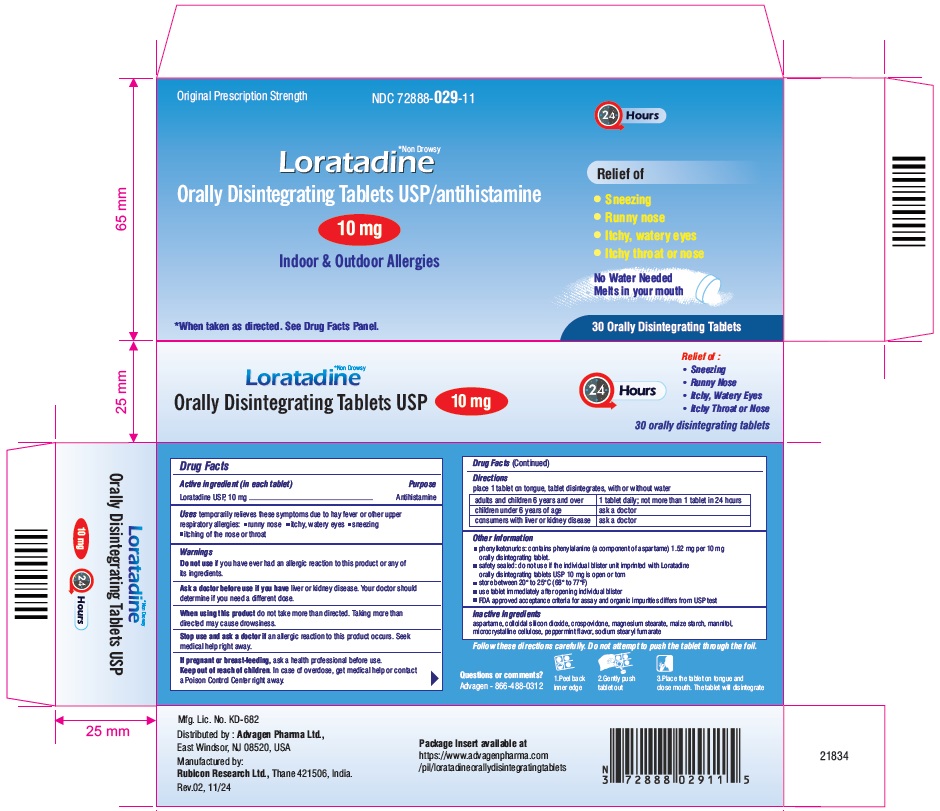 DRUG LABEL: LORATADINE
NDC: 72888-029 | Form: TABLET, ORALLY DISINTEGRATING
Manufacturer: Advagen Pharma Limited
Category: otc | Type: HUMAN OTC DRUG LABEL
Date: 20260105

ACTIVE INGREDIENTS: LORATADINE 10 mg/1 1
INACTIVE INGREDIENTS: ASPARTAME; SILICON DIOXIDE; CROSPOVIDONE; MAGNESIUM STEARATE; STARCH, CORN; MANNITOL; MICROCRYSTALLINE CELLULOSE; SODIUM STEARYL FUMARATE

Drug Facts

Active ingredient (in each tablet) Purpose

Loratadine USP, 10 mg………………………………….....................Antihistamine

Usestemporarily relieves these symptoms due to hay fever or other upper respiratory allergies: ■ runny nose ■ itchy, watery eyes ■ sneezing ■ itching of the nose or throat

Warnings
Do not useif you have ever had an allergic reaction to this product or any of its ingredients.

Ask a doctor before use if you haveliver or kidney disease. Your doctor should determine if you need a different dose.

When using a productdo not take more than directed. Taking more than directed may cause drowsiness.

Stop use and ask a doctor ifan allergic reaction to this product occurs.
Seek medical help right away.

If pregnant or breast-feeding,ask a health professional before use.
Keep out of reach of children.In case of overdose, get medical help or contact a Poison Control Center right away.

Directions

- place 1 tablet on tongue; tablet disintegrates, with or without water

adults and children 6 years and over

1 tablet daily; not more than 1 tablet in 24 hours

Children under 6 years of age

ask a doctor

Consumers with liver or kidney disease

ask a doctor

Other information

- Phenylketonurics: contains phenylalanine (a component of aspartame) 1.52 mg per 10 mg orally disintegrating tablet.
- safety sealed: do not use if the individual blister unit imprinted with Loratadine Orally Disintegrating Tablets USP 10 mg is open or torn
- store between 20° to 25°C (68° to 77°F)
- use tablet immediately after opening individual blister
- FDA approved acceptance criteria for assay and organic impurities differs from USP test

Inactive ingredients

aspartame, colloidal silicon dioxide, crospovidone, magnesium stearate, maize starch, mannitol, microcrystalline cellulose, peppermint flavor, sodium stearyl fumarate

Questions or comments?
Advagen - 866-488-0312

Distributed by:
Advagen Pharma Ltd
East Windsor, NJ 08520, USA

Manufactured by:
Rubicon Research Ltd.,
Thane 421506, India.

Rev. 02, 11/24

Note:Imprint Code - Λ indicated as UpArrowhead in Drug Listing Data Element (DLDE) section.

PRINCIPAL DISPLAY PANEL

Loratadine Orally Disintegrating Tablets USP 10 mg - 10 Tablets - NDC 72888-029-09

Loratadine Orally Disintegrating Tablets USP 10 mg - 30 Tablets - NDC 72888-029-11